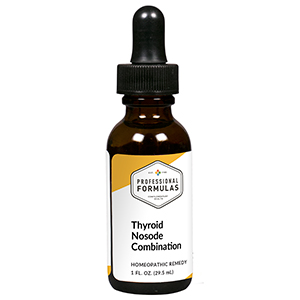 DRUG LABEL: Thyroid Nosode Combination
NDC: 63083-9420 | Form: LIQUID
Manufacturer: Professional Complementary Health Formulas
Category: homeopathic | Type: HUMAN OTC DRUG LABEL
Date: 20190815

ACTIVE INGREDIENTS: COLCHICUM AUTUMNALE BULB 4 [hp_X]/29.5 mL; FUCUS VESICULOSUS 6 [hp_X]/29.5 mL; SPONGIA OFFICINALIS SKELETON, ROASTED 6 [hp_X]/29.5 mL; OXOGLURIC ACID 8 [hp_X]/29.5 mL; FUMARIC ACID 8 [hp_X]/29.5 mL; MALIC ACID 8 [hp_X]/29.5 mL; SODIUM DIETHYL OXALACETATE 8 [hp_X]/29.5 mL; PULSATILLA MONTANA WHOLE 8 [hp_X]/29.5 mL; HYSSOPUS OFFICINALIS WHOLE 8 [hp_X]/29.5 mL; CALCIUM FLUORIDE 10 [hp_X]/29.5 mL; THYROID, UNSPECIFIED 12 [hp_X]/29.5 mL
INACTIVE INGREDIENTS: ALCOHOL; WATER

R420

ACTIVE INGREDIENTS

Colchicum autumnale 4X
Fucus vesiculosus 6X
Spongia tosta 6X
a-Ketoglutaricum acidum 8X
Fumaricum acidum 8X
Malicum acidum 8X
Natrum oxalaceticum 8X
Pulsatilla 8X
Thymus 8X
Calcarea fluorica 10X
Thyroidinum 12X

QUESTIONS

Professional Formulas

PO Box 2034 Lake Oswego, OR 97035

INDICATIONS

For the temporary relief of occasional headache, cough, minor abdominal or back pain, flatulence, nausea, or dry, itchy skin.*

PURPOSE

*Claims based on traditional homeopathic practice, not accepted medical evidence. Not FDA evaluated.

WARNINGS

Persistent symptoms may be a sign of a serious condition. If symptoms persist or are accompanied by a fever, rash, or persistent headache, consult a doctor. Keep out of the reach of children. In case of overdose, get medical help or contact a poison control center right away. If pregnant or breastfeeding, ask a healthcare professional before use.

Keep out of the reach of children.

PREGNANCY OR BREAST FEEDING

If pregnant or breastfeeding, ask a healthcare professional before use.

DIRECTIONS

Place drops under tongue 30 minutes before/after meals. Adults and children 12 years and over: Take 10 to 15 drops once weekly or monthly. If mild symptoms are present, take 10 drops up to 3 times per day. Consult a physician for use in children under 12 years of age.

OTHER INFORMATION

Tamper resistant. If seal is broken, do not use. After opening, close container tightly and store at room temperature away from heat.

INACTIVE INGREDIENTS

40% ethanol, purified water.

LABEL

Est 1985

Professional Formulas

Complementary Health

Thyroid Nosode Combination

Homeopathic Remedy

1 FL. OZ. (29.5 mL)